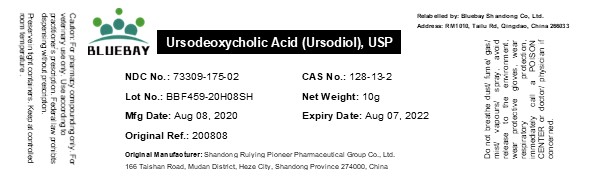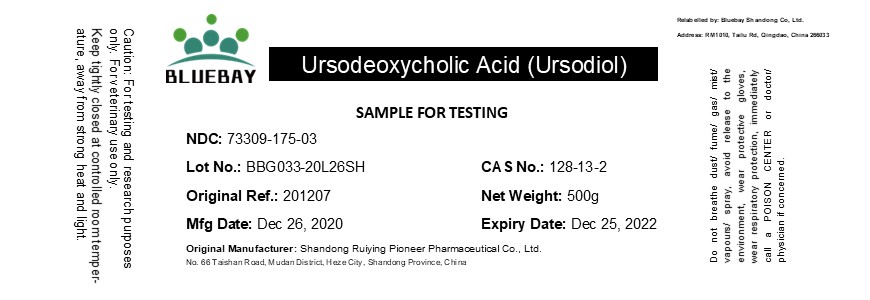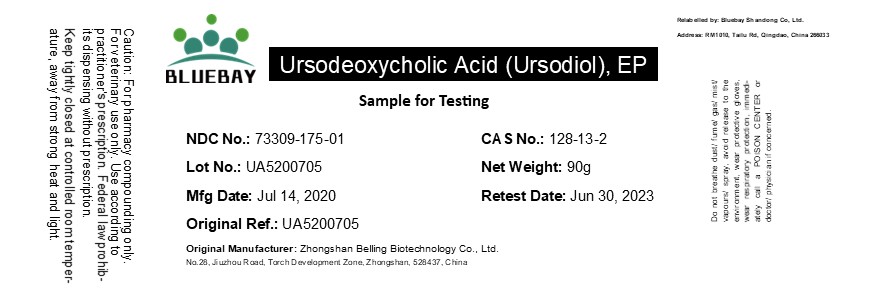 DRUG LABEL: Ursodeoxycholic Acid (Ursodiol)
NDC: 73309-175 | Form: POWDER
Manufacturer: BLUEBAY SHANDONG CO.,LTD
Category: other | Type: BULK INGREDIENT
Date: 20210708

ACTIVE INGREDIENTS: URSODIOL 1 g/1 g

Ursodeoxycholic Acid (Ursodiol)